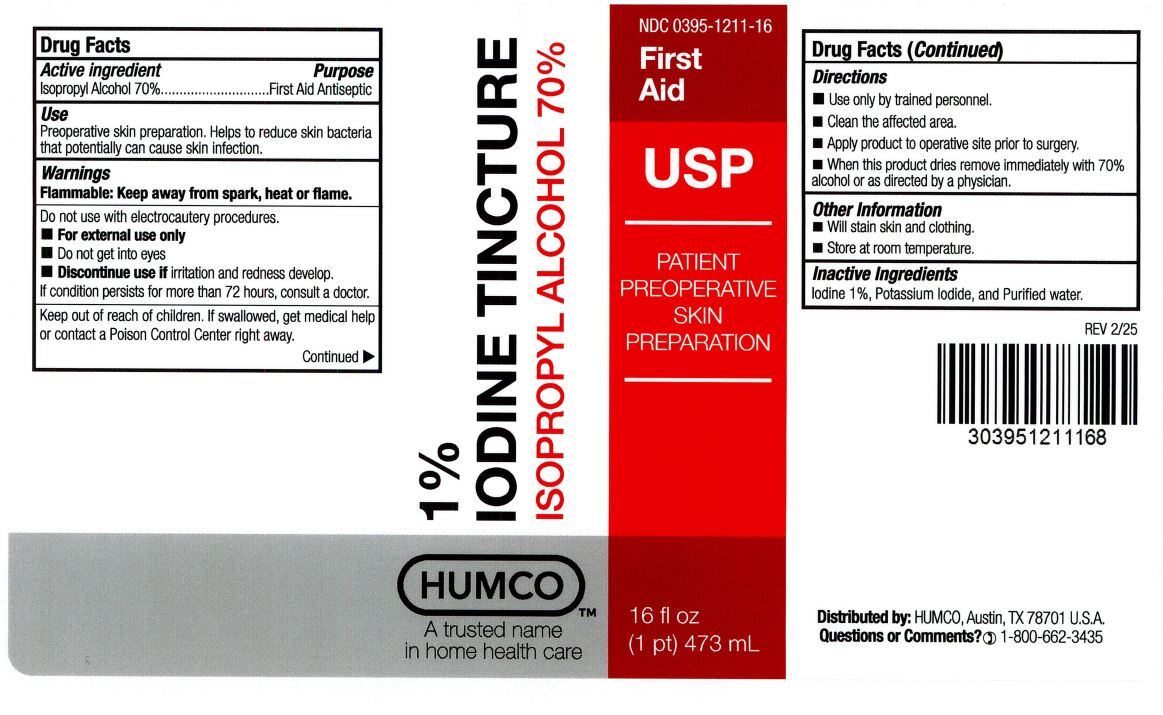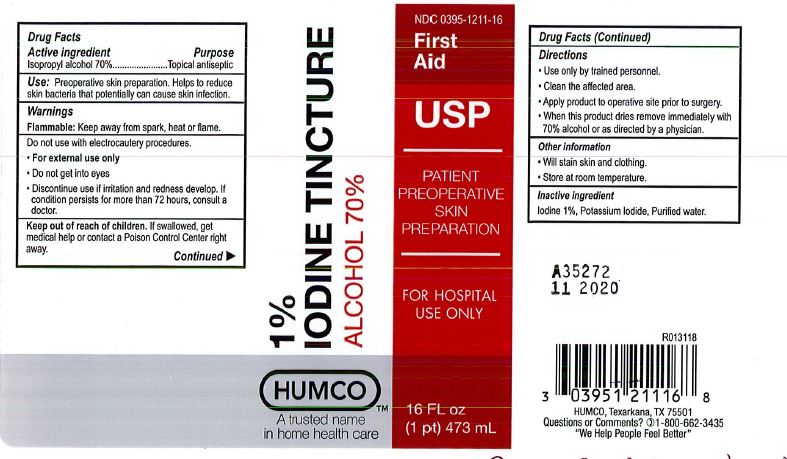 DRUG LABEL: HUMCO 1 Percent Iodine
NDC: 0395-1211 | Form: LIQUID
Manufacturer: Humco Holding Group, Inc.
Category: otc | Type: HUMAN OTC DRUG LABEL
Date: 20250922

ACTIVE INGREDIENTS: ISOPROPYL ALCOHOL 700 mg/1 mL
INACTIVE INGREDIENTS: IODINE 10 mg/1 mL; POTASSIUM IODIDE; WATER

Iodine Tincture 1 percent

HUMCO 1% Iodine Tincture

Drug Facts

Active Ingredient

Isopropyl Alcohol 70%

Purpose

Topical antiseptic

Indications

Preoperative skin preparation. Helps to reduce skin bacteria that potentially can cause skin infection.

Warnings:

Flammable:Keep away from spark, heat or flame.

Do not use with electrocautery procedures.

For external use only.

Do not use

in the eyes

Discontinue use if irritation and redness develop. If condition persists for more than 72 hours, consult a doctor.

IF ON SKIN:Wash with plenty of soap and water.

IF IN EYES:Rinse cautiously with water for several minutes. Remove contact lenses, if present and easy to do. Continue rinsing. If skin irritation or rash occurs of if eye irritation persists, get medical advice/attention. Take off contaminated clothing and wash before reuse.

IN CASE OF FIRE:Use dry sand, dry chemical or alcohol resistant foam to extinguish. Store in well ventilated place. Keep cool. Dispose contents/container to an approved waste disposal plant.

Keep out of reach of children.

If swallowed get medical help or contact a Poison Control Center right away.

Directions

- Use only by trained personnel.
- Clean the affected area.
- Apply product to operative site prior to surgery.
- When this product dries remove immediately with 70% alcohol or as directed by a physician.

Other Information

Will stain skin and clothing. Store at room temperature.

Inactive Ingredient

Iodine 1%, Potassium iodide, Purified water.